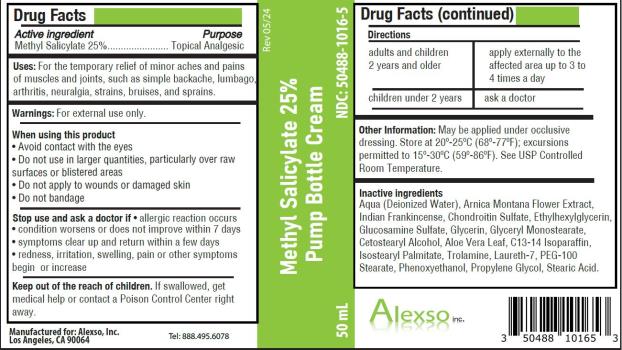 DRUG LABEL: Methyl Salicylate 25 Percent
NDC: 50488-1016 | Form: CREAM
Manufacturer: Alexso, Inc
Category: otc | Type: HUMAN OTC DRUG LABEL
Date: 20240523

ACTIVE INGREDIENTS: METHYL SALICYLATE 250 mg/1 mL
INACTIVE INGREDIENTS: WATER; ARNICA MONTANA FLOWER; INDIAN FRANKINCENSE; CHONDROITIN SULFATE (BOVINE); ETHYLHEXYLGLYCERIN; GLUCOSAMINE SULFATE; GLYCERYL MONOSTEARATE; CETOSTEARYL ALCOHOL; ALOE VERA LEAF; C13-14 ISOPARAFFIN; ISOSTEARYL PALMITATE; TROLAMINE; LAURETH-7; PEG-100 STEARATE; PHENOXYETHANOL; PROPYLENE GLYCOL; STEARIC ACID

Methyl Salicylate 25_Percent Pump Cream

Methyl Salicylate 25% Pump Bottle Cream

Drug Facts

Active ingredient

Methyl Salicylate 25%

Purpose

Topical analgesic

Uses

For the temporary relief of minor aches and pains of muscles and joints, such as simple backache, lumbago, arthritis, neuralgia, strains, bruises, and sprains.

Warnings

For external use only.

When using this product

- Avoid contact with the eyes
- Do not use in large quantities, particularly over raw surfaces or blistered areas
- Do not apply to wounds or damaged skin
- Do not bandage

Stop use and ask a doctor if

- allergic reaction occurs
- condition worsens or does not improve within 7 days
- symptoms clear up and return within a few days
- redness, irritation, swelling, pain or other symptoms begin or increase

Keep out of reach of children.

If swallowed, get medical help or contact a Poison Control Center right away.

Directions

adults and children 2 years and older | apply externally to the affected area up to 3 to 4 times a day
children under 2 years | ask a doctor

Other information

- May be applied under occlusive dressing.
- Store at 20-25°C (68-77°F); excursions permitted to 15-30°C (59-86°F). See USP Controlled Room Temperature.

Inactive ingredients

Aqua (Deionized Water), Arnica Montana Flower Extract, Indian Frankincense, Chondroitin Sulfate, Ethylhexylglycerin, Glucosamine Sulfate, Glycerin, Glyceryl Monostearate, Cetostearyl Alcohol, Aloe Vera Leaf, C13-14 Isoparaffin, Isostearyl Palmitate, Trolamine, Laureth-7, PEG-100 Stearate, Phenoxyethanol, Propylene Glycol, Stearic Acid.

Methyl Salicylate 25% Pump Bottle Cream

NDC: 50488-1016-5

50 mL

Manufactured for:
Alexso, Inc
Los Angeles, CA 90064

Tel: 888.495.6078

PRINCIPAL DISPLAY PANEL

NDC 50488-1016-5
Methyl Salicylate 25% Pump Bottle Cream
50 mL

Rev 05/24